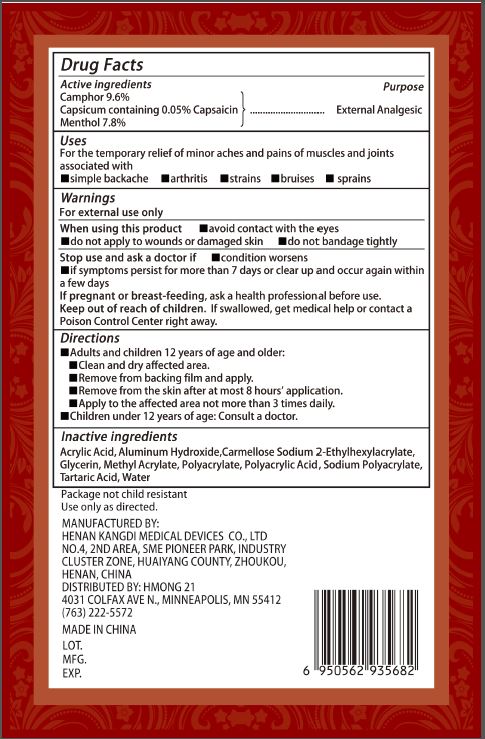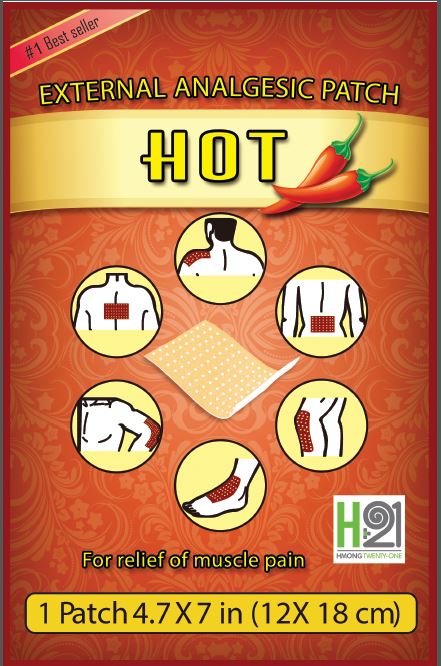 DRUG LABEL: EXTERNAL ANALGESIC
NDC: 70927-001 | Form: PATCH
Manufacturer: Hmong 21
Category: otc | Type: HUMAN OTC DRUG LABEL
Date: 20231226

ACTIVE INGREDIENTS: CAMPHOR (SYNTHETIC) 96 mg/1 g; CAPSAICIN 0.5 mg/1 g; MENTHOL 78 mg/1 g
INACTIVE INGREDIENTS: ALUMINUM HYDROXIDE; GLYCERIN; METHYL ACRYLATE; TARTARIC ACID; WATER; CAPSICUM

EXTERNAL ANALGESIC

Active ingredients

Camphor 9.6%

Capsaicin 0.05%

Menthol 7.8%

Purpose

External Analgesic

Uses

For the temporary relief of minor aches and pains of muscles and joints associated with

-simple backache

-arthritis

-strains

-bruises

-sprains

Warnings

When using this product

-avoid contact with the eyes

- do not apply to wounds or damaged skin

-do not bandage tightly

Stop use and ask a doctor if

- condition worsens

-if synthoms oersust for more than 7 days or clear up and occur again within a few days

If pregnant or breast-feeding, ask a health professional before use.

Keep out of reach of children.

If Swallowed, get medical help or contact a Poison Control Center right away.

Directions

Adults and children 12 years of age and older:

-Clean and dry affected area.

-Remove from backing film and apply.

-Remove from the skin after at most 8 hours' application.

-Apply to the affected area not more than 3 times daily.

-Children under 12 years of age: Consult a doctor.

Inactive ingredients

Acrylic Acid, Aluminum Hydroxide, Carmellose Sodium, 2-ethylhexylacrylate, Glycerin, Methyl Acrylate, Polyacrylate, polyacrylic Acid, sodium polyacrylatem, Tartaric Acid, Water.